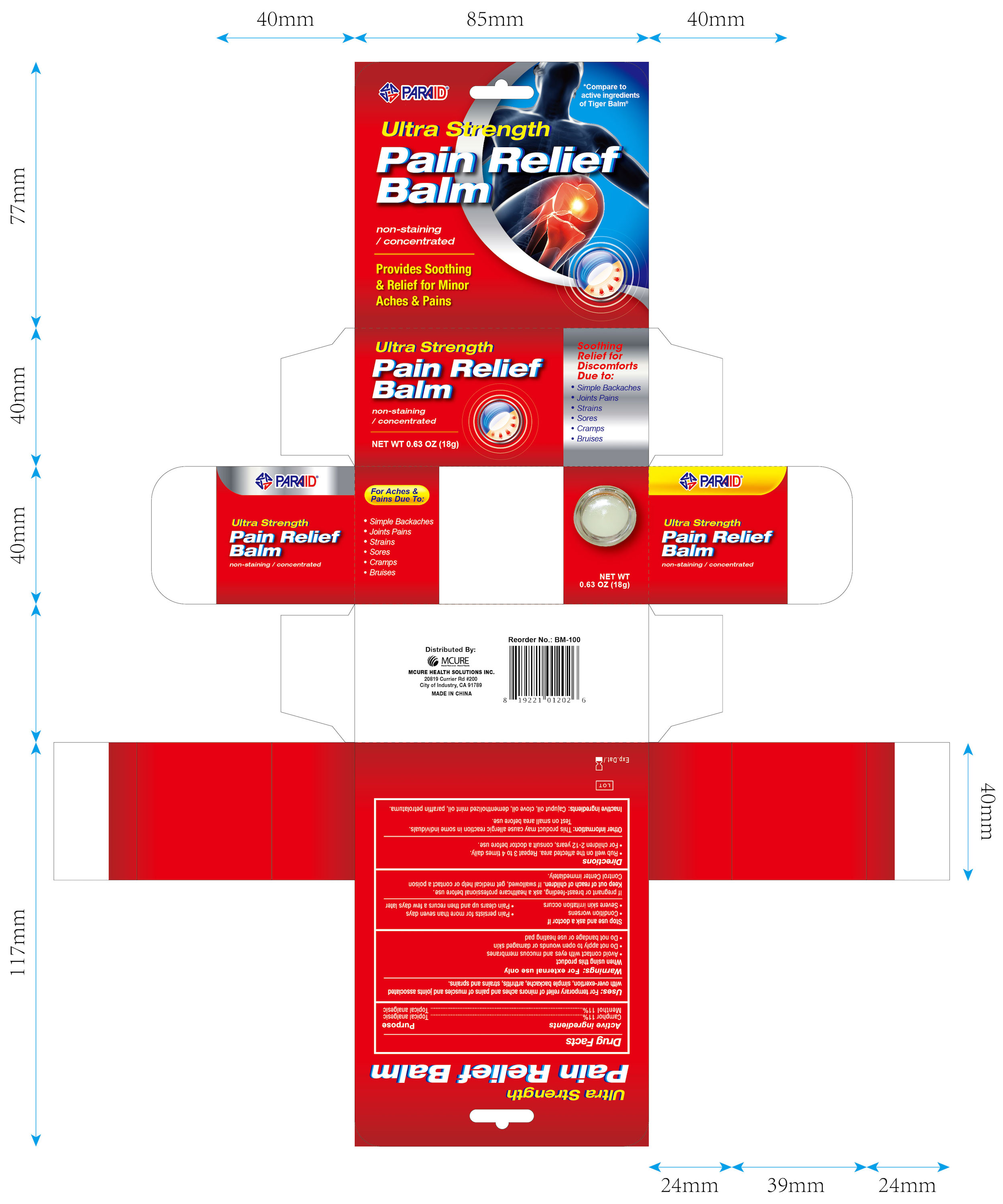 DRUG LABEL: ULTRA STRENGTH PAIN RELIEF BALM
NDC: 71183-320 | Form: OINTMENT
Manufacturer: Suzhou Vastech Medical Technology Co., Ltd
Category: otc | Type: HUMAN OTC DRUG LABEL
Date: 20170320

ACTIVE INGREDIENTS: MENTHOL 11 g/100 g; CAMPHOR (SYNTHETIC) 11 g/100 g
INACTIVE INGREDIENTS: PETROLATUM; PARAFFIN; CAJUPUT OIL; CLOVE OIL

Active ingredients Purpose

Camphor 11%........................................................ Topical analgesic

Menthol 11%.......................................................... Topical analgesic

Uses

For temporary relief of minor aches and pains of muscles and joints associated with over-exertion, simple backache, arhtritis, strains, and sprains.

Warnings

For external use only.

When using this product

- Avoid contact with the eyes and mucous membranes
- Do not apply to open wounds or damaged skin
- Do not bandage or use heating pad

Stop use and ask a doctor if

- Condition worsens
- Severe skin irritation occurs
- Pain persists for more than seven days
- Pain clears up and then recurs a few days later

PREGNANCY

If pregnant or breast feeding, ask a healthcare professional before use.

Keep out of reach of children.

If swallowed get medical help or contact a Poison Control Center immediately.

Directions

- Rub well on the affected area. Repeat 3 to 4 times dailys.
- For children 2-12 years, consult a doctor before use.

Other information

This product may cause allergic reaction in some individuals. Test on small area before use.

Inactive ingredients

cajuput oil, clove oil, dementholized mint oil, paraffin petrolatuma

DOSAGE AND ADMINISTRATION

Distributed by:

MCURE HEALTH SOLUTIONS INC.

20819 Currier Rd #200

City of Industry, CA 91789

Made in China